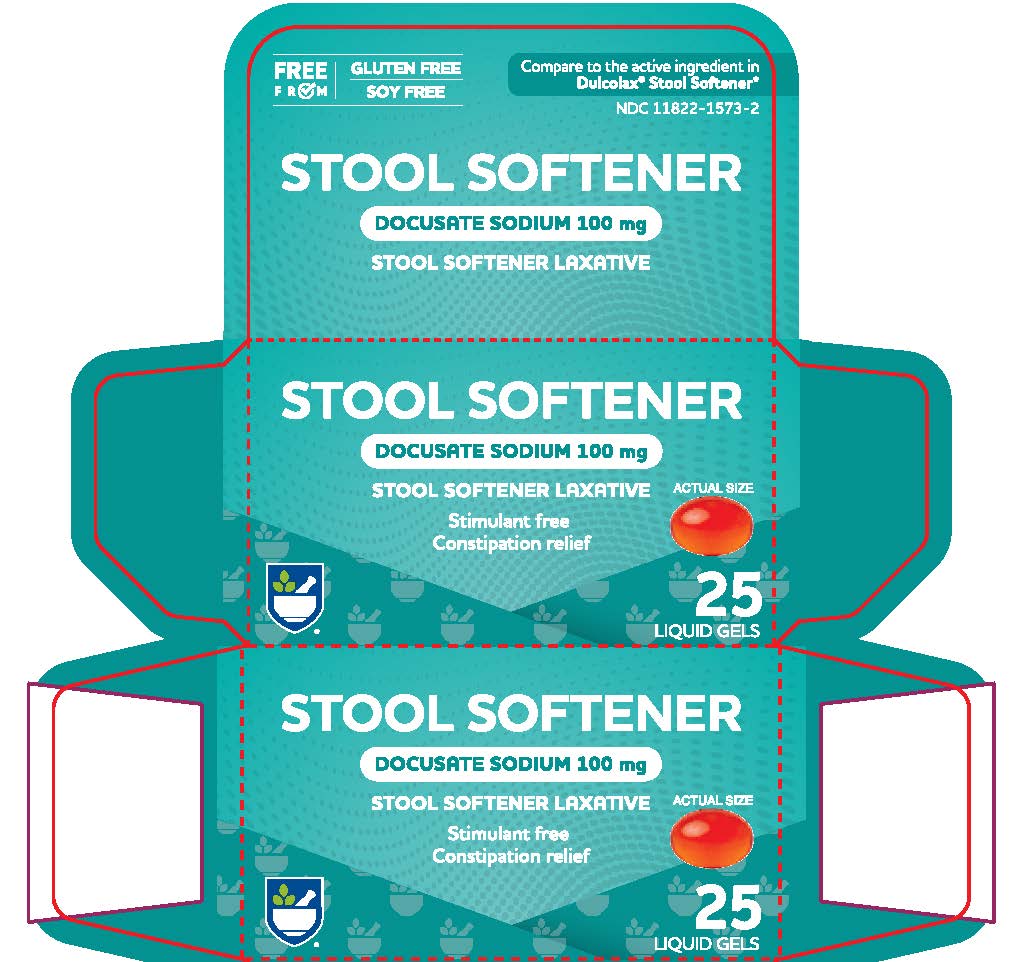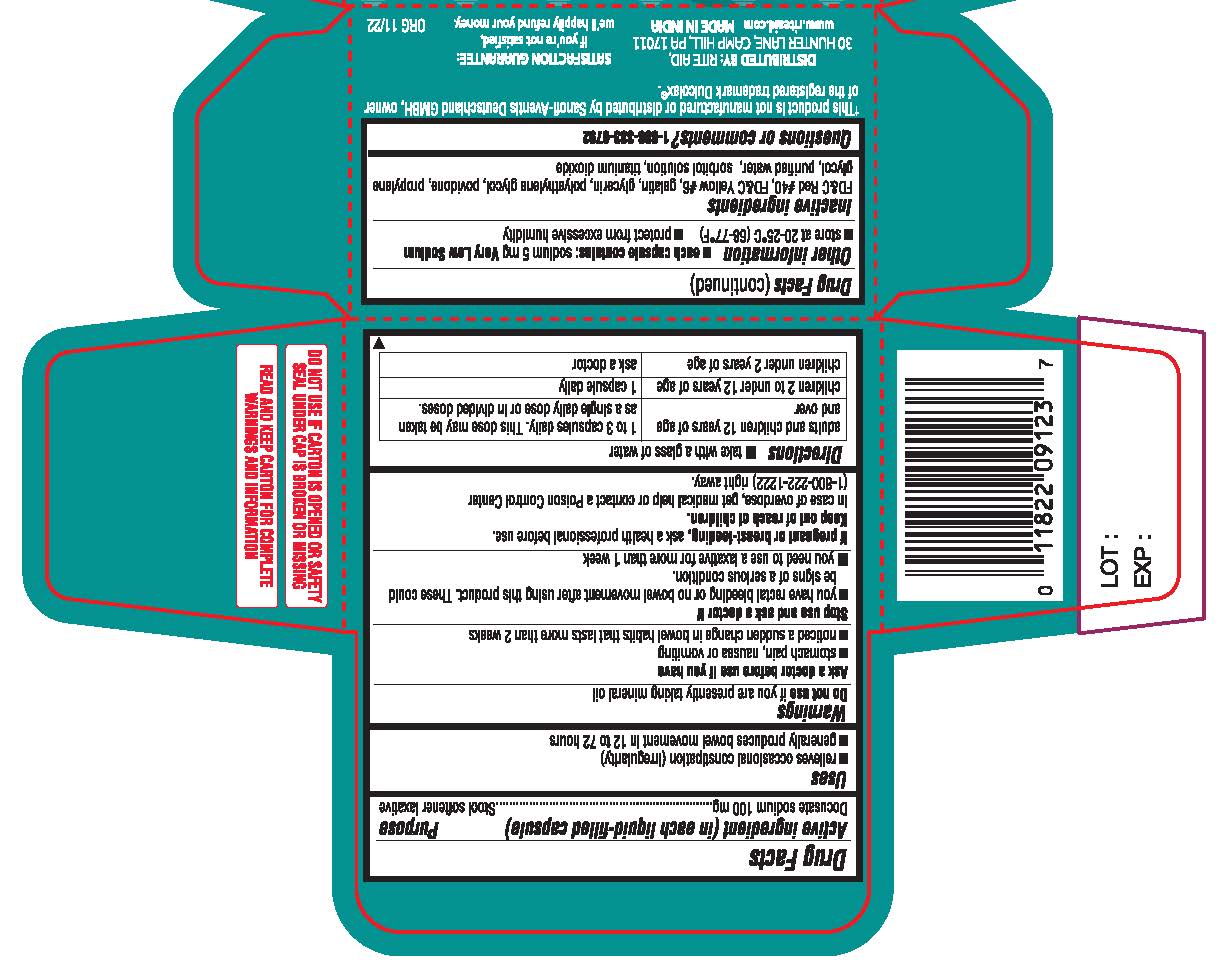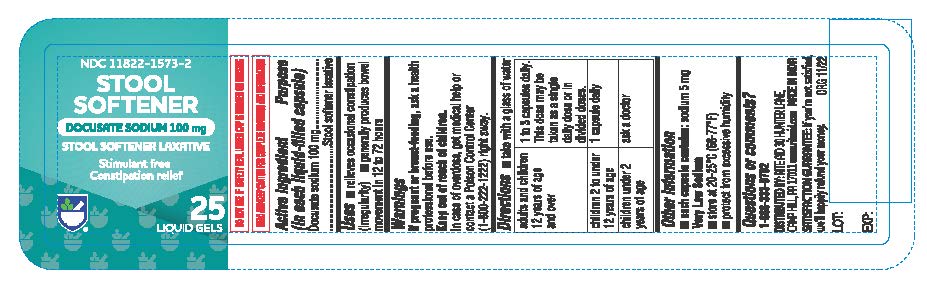 DRUG LABEL: Gentle Stool softener
NDC: 11822-1573 | Form: CAPSULE, LIQUID FILLED
Manufacturer: RITE AID CORPORATION
Category: otc | Type: HUMAN OTC DRUG LABEL
Date: 20241230

ACTIVE INGREDIENTS: DOCUSATE SODIUM 100 mg/1 1
INACTIVE INGREDIENTS: FD&C RED NO. 40; FD&C YELLOW NO. 6; GELATIN; GLYCERIN; POLYETHYLENE GLYCOL 400; POVIDONE; PROPYLENE GLYCOL; WATER; SORBITOL SOLUTION; TITANIUM DIOXIDE

Gentle Stool Softener

Active Ingredient (in each tablet)

Docusate sodium 100 mg

Purpose

Stool softener

Uses

• relieves occasional constipation (irregularity) • generally produces bowel movement in 12–72 hours

Warnings

Do not use if you are presently taking mineral oil, unless told to do so by a doctor

Ask a doctor before use if you have • fever • mucus in the stool

Ask a doctor or pharmacist before use if you are if you have
• stomach pain • nausea • vomiting • noticed a sudden change in bowel habits that lasts over 2 weeks

Stop use and ask a doctor if • you have rectal bleeding or fail to have a bowel movement after use of a laxative. These could be signs of a serious condition • you need to use a stool softener
laxative for more than 1 week

PREGNANCY OR BREAST FEEDING

If pregnant or breast-feeding, ask a health professional before use.

Keep out of reach of children. In case of overdose, get medical help or contact a Poison Control Center right away. (1-800-222-1222)

Directions

• take only by mouth. Doses may be taken as a single daily dose or in divided doses.

adults & children 12 years of age & over | take 1–3 softgels daily
children 2 to under 12 years of age | take 1 softgel daily
children under 2 years of age | ask a doctor

Other information

• store at 25°C (77°F); excursions permitted between 15°–30°C (59°–86°F) • Keep tightly closed

Inactive ingredients

FD&C Red #40, FD&C Yellow #6, gelatin, glycerin, polyethylene glycol-400, povidone, propylene glycol, purified water, sorbitol solution, titanium dioxide

Questions or comments?

1-888-333-9792